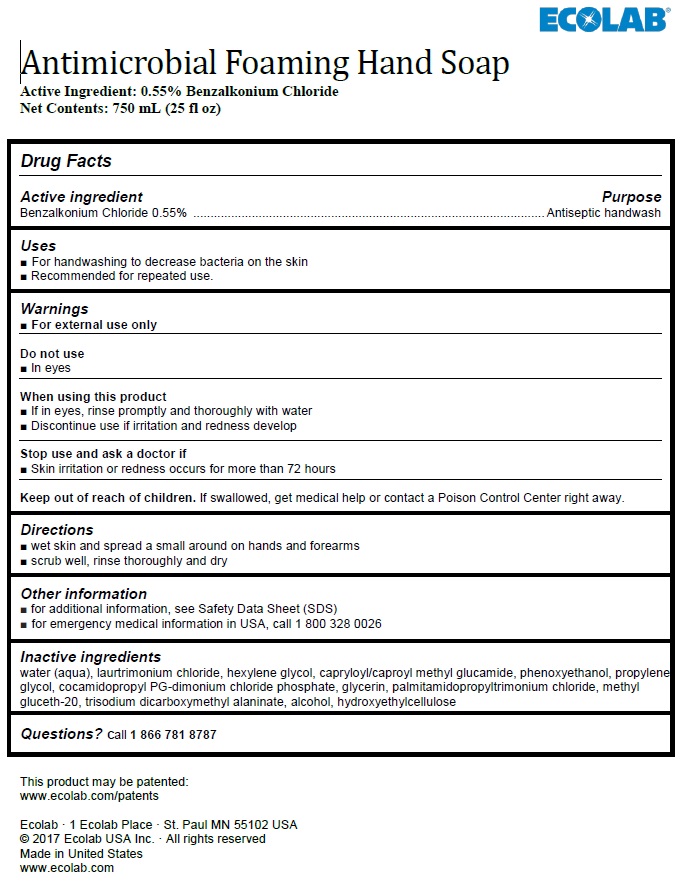 DRUG LABEL: Ecolab
NDC: 47593-593 | Form: SOLUTION
Manufacturer: Ecolab Inc.
Category: otc | Type: HUMAN OTC DRUG LABEL
Date: 20240805

ACTIVE INGREDIENTS: BENZALKONIUM CHLORIDE 5.5 mg/1 mL
INACTIVE INGREDIENTS: WATER; LAURTRIMONIUM CHLORIDE; HEXYLENE GLYCOL; DECANOYL N-METHYLGLUCAMIDE; PHENOXYETHANOL; PROPYLENE GLYCOL; COCAMIDOPROPYL PROPYLENE GLYCOL-DIMONIUM CHLORIDE PHOSPHATE; GLYCERIN; PALMITAMIDOPROPYLTRIMONIUM CHLORIDE; METHYL GLUCETH-20; TRISODIUM DICARBOXYMETHYL ALANINATE; ALCOHOL; HYDROXYETHYL CELLULOSE (2000 MPA.S AT 1%)

Drug Facts

Active ingredient

Benzalkonium Chloride, 0.55%

Purpose

Antiseptic handwash

Uses

- For handwashing to decrease bacteria on the skin
- Recommended for repeated use.

Warnings

- For external use only

Do not use

- In eyes

When using this product

- If in eyes, rinse promptly and thoroughly with water
- Discontinue use if irritation and redness develop

Stop use and ask a doctor if

- Skin irritation or redness occurs for more than 72 hours

Keep out of reach of children. If swallowed, get medical help or contact a Poison Control Center right away.

Directions

- wet skin and spread a small around on hands and forearms
- scrub well, rinse thoroughly and dry

Other information

- for additional information, see Safety Data Sheet (SDS)
- for emergency medical information in USA, call 1 800 328 0026

INACTIVE INGREDIENT

Inactive ingredients water (aqua), laurtrimonium chloride, capryloyl/caproyl methyl glucamide, phenoxyethanol, propylene glycol, cocamidopropyl PG-dimonium chloride phosphate, glycerin, palmitamidopropyltrimonium chloride, methyl gluceth-20, trisodium dicarboxymethyl alaninate, alcohol, hydroxyethylcellulose

Questions? call 1 866 781 8787

Prinicpal Display Panel / Representative Label

ECOLAB®

Antimicrobial Foaming Hand Soap
Active Ingredient: 0.55% Benzalkonium Chloride
Net Contents: 750 mL (25 fl oz)

This product may be patented:
www.ecolab.com/patents

Ecolab · 1 Ecolab Place · St. Paul MN 55102 USA
© 2017 Ecolab USA Inc. · All rights reserved
Made in United States
www.ecolab.com